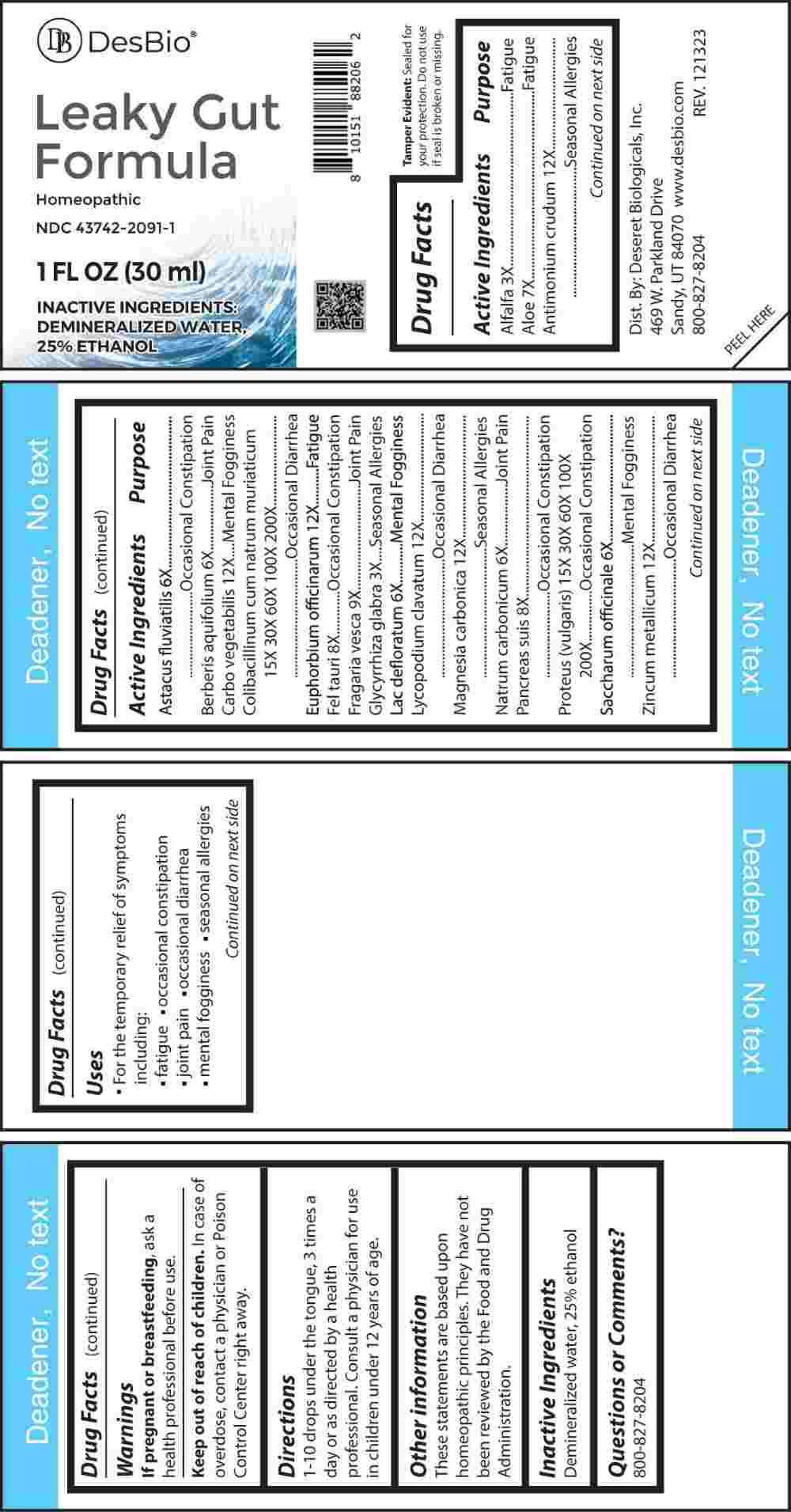 DRUG LABEL: Leaky Gut Formula
NDC: 43742-2091 | Form: LIQUID
Manufacturer: Deseret Biologicals, Inc.
Category: homeopathic | Type: HUMAN OTC DRUG LABEL
Date: 20240314

ACTIVE INGREDIENTS: MEDICAGO SATIVA WHOLE 3 [hp_X]/1 mL; GLYCYRRHIZA GLABRA 3 [hp_X]/1 mL; ASTACUS ASTACUS 6 [hp_X]/1 mL; BERBERIS AQUIFOLIUM ROOT BARK 6 [hp_X]/1 mL; SKIM MILK 6 [hp_X]/1 mL; SODIUM CARBONATE 6 [hp_X]/1 mL; SUCROSE 6 [hp_X]/1 mL; ALOE 7 [hp_X]/1 mL; BOS TAURUS BILE 8 [hp_X]/1 mL; SUS SCROFA PANCREAS 8 [hp_X]/1 mL; FRAGARIA VESCA FRUIT 9 [hp_X]/1 mL; ANTIMONY TRISULFIDE 12 [hp_X]/1 mL; ACTIVATED CHARCOAL 12 [hp_X]/1 mL; EUPHORBIA RESINIFERA RESIN 12 [hp_X]/1 mL; LYCOPODIUM CLAVATUM SPORE 12 [hp_X]/1 mL; MAGNESIUM CARBONATE 12 [hp_X]/1 mL; ZINC 12 [hp_X]/1 mL; ESCHERICHIA COLI 15 [hp_X]/1 mL; PROTEUS INCONSTANS 15 [hp_X]/1 mL
INACTIVE INGREDIENTS: WATER; ALCOHOL

DRUG FACTS:

ACTIVE INGREDIENTS:

Alfalfa 3X, Aloe 7X, Antimonium Crudum 12X, Astacus Fluviatilis 6X, Berberis Aquifolium 6X, Carbo Vegetabilis 12X, Colibacillinum Cum Natrum Muriaticum 15X, 30X, 60X, 100X, 200X, Euphorbium Officinarum 12X, Fel Tauri 8X, Fragaria Vesca 9X, Glycyrrhiza Glabra 3X, Lac Defloratum 6X, Lycopodium Clavatum 12X, Magnesia Carbonica 12X, Natrum Carbonicum 6X, Pancreas Suis 8X, Proteus (Vulgaris) 15X, 30X, 60X, 100X, 200X, Saccharum Officinale 6X, Zincum Metallicum 12X.

PURPOSE:

Alfalfa – Fatigue, Aloe - Fatigue, Antimonium Crudum – Seasonal Allergies, Astacus Fluviatilis – Occasional Constipation, Berberis Aquifolium – Joint Pain, Carbo Vegetabilis – Mental Fogginess, Colibacillinum Cum Natrum Muriaticum – Occasional Diarrhea, Euphorbium Officinarum – Fatigue, Fel Tauri – Occasional Constipation, Fragaria Vesca – Joint Pain, Glycyrrhiza Glabra – Seasonal Allergies, Lac Defloratum – Mental Fogginess, Lycopodium Clavatum – Occasional Diarrhea, Magnesia Carbonica – Seasonal Allergies, Natrum Carbonicum – Joint Pain, Pancreas Suis – Occasional Constipation, Proteus (Vulgaris) – Occasional Constipation, Saccharum Officinale – Mental Fogginess, Zincum Metallicum – Occasional Diarrhea

USES:

• For the temporary relief of symptoms including:

• fatigue • occasional constipation • joint pain

• occasional diarrhea • mental fogginess • seasonal allergies

These statements are based upon homeopathic principles. They have not been reviewed by the Food and Drug Administration.

WARNINGS:

If pregnant or breast-feeding, ask a health professional before use.

Keep out of reach of children. In case of overdose, contact a physician or Poison Control Center right away.

Tamper Evident: Sealed for your protection. Do not use if seal is broken or missing.

KEEP OUT OF REACH OF CHILDREN:

In case of overdose, contact a physician or Poison Control Center right away.

DIRECTIONS:

1-10 drops under the tongue, 3 times a day or as directed by a health professional. Consult a physician for use in children under 12 years of age.

INACTIVE INGREDIENTS:

Demineralized water, 25% ethanol

QUESTIONS:

Dist. By: Deseret Biologicals, Inc.

469 W. Parkland Drive

Sandy, UT 84070

www.desbio.com

800-827-8204

PACKAGE LABEL DISPLAY:

Des Bio

Leaky Gut

Formula

Homeopathic

NDC 43742-2091-1

1 FL OZ (30 ml)